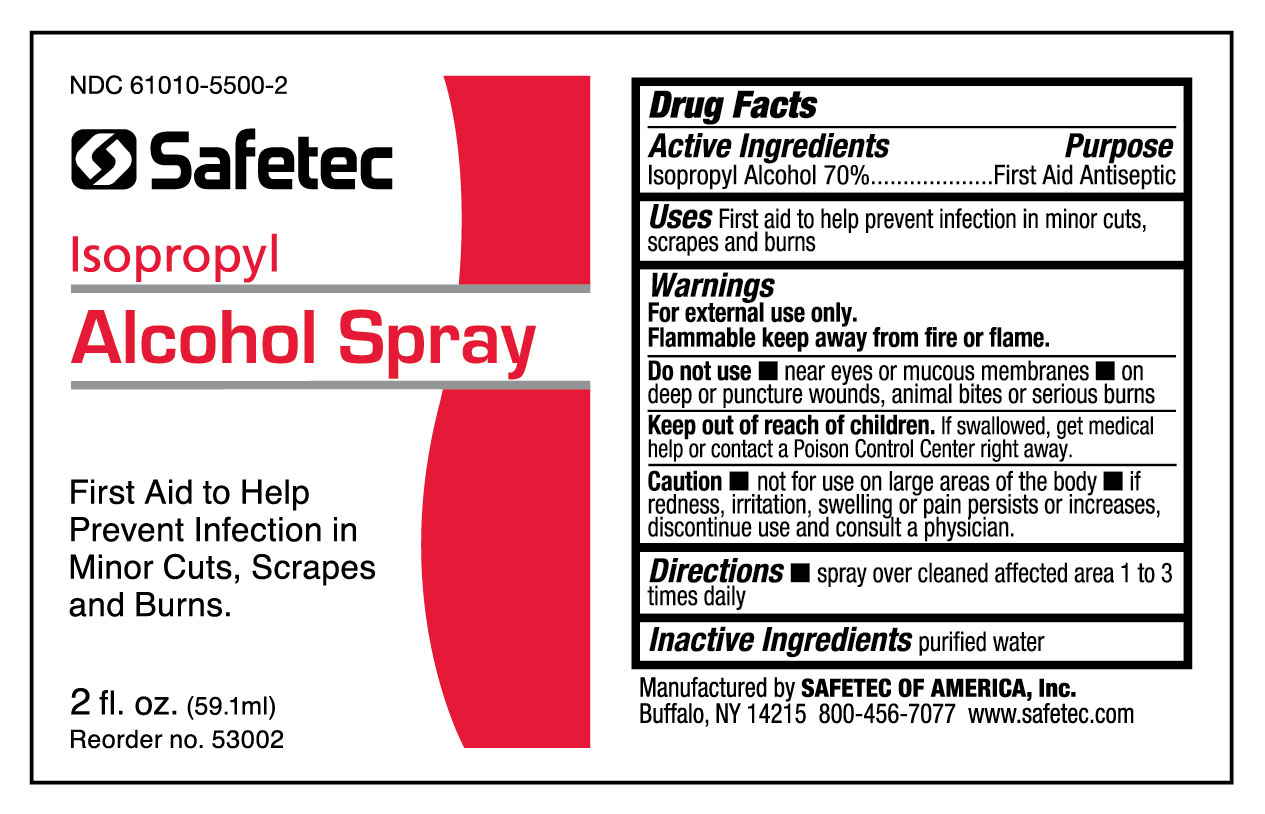 DRUG LABEL: Isopropyl Alcohol
NDC: 61010-5500 | Form: SPRAY
Manufacturer: Safetec of America, Inc.
Category: otc | Type: HUMAN OTC DRUG LABEL
Date: 20250808

ACTIVE INGREDIENTS: ISOPROPYL ALCOHOL 70 mL/100 mL
INACTIVE INGREDIENTS: WATER

Isopropyl alcohol, 70% 2oz. Bottle

Drug Facts

Active Ingredients

Isopropyl Alcohol 70.0%

Purpose

First Aid Antiseptic

Uses

First aid to help prevent infection in minor cuts, scrapes and burns

Warnings

For external use only.

Flammable keep away from fire or flame.

Do not use

- near eyes or mucous membranes
- on deep or puncture wounds, animal bites, or serious burns

Keep out of reach of children.

Caution

- not for use on large areas of the body
- if redness, irritation, swelling or pain persists or increases, discontinue use and consult a physician

Directions

- spray over cleaned affected area 1 to 3 times daily

Inactive ingredients

purified water

PRINCIPAL DISPLAY PANEL – 2 oz. bottle label

NDC 61010-5500-2

Safetec

Isopropyl
Alcohol Spray

First Aid to Help
Prevent Infection in
Minor Cuts, Scrapes
and Burns.

2 fl. oz. (59.1ml)
Reorder no. 53002